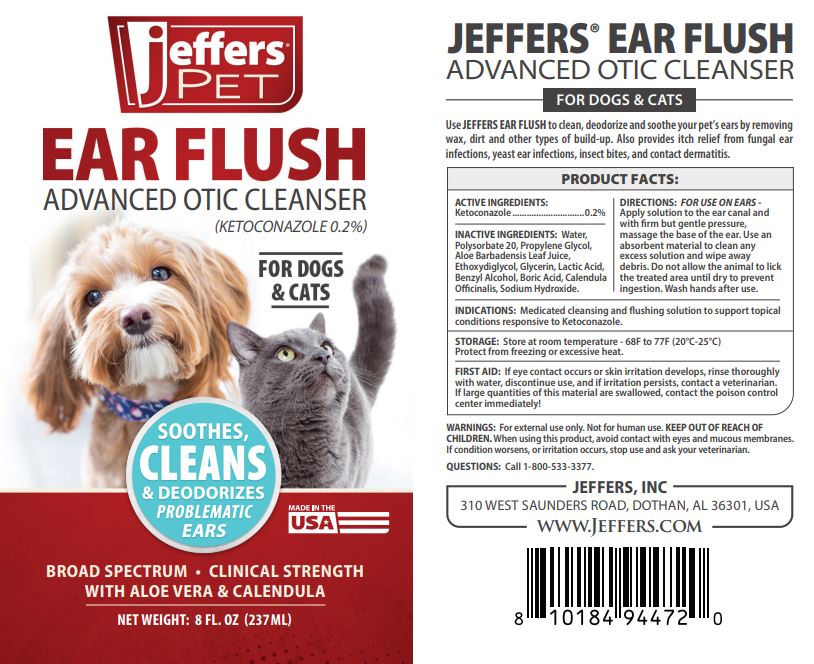 DRUG LABEL: JEFFERS EAR FLUSH - ADVANCED OTIC CLEANSER
NDC: 86010-300 | Form: LIQUID
Manufacturer: JEFFERS
Category: animal | Type: OTC ANIMAL DRUG LABEL
Date: 20250401

ACTIVE INGREDIENTS: KETOCONAZOLE 2 g/1000 g
INACTIVE INGREDIENTS: WATER; POLYSORBATE 20; PROPYLENE GLYCOL; ALOE BARBADENSIS LEAF; ETHOXYDIGLYCOL; GLYCERIN; LACTIC ACID; BENZYL ALCOHOL; CALENDULA OFFICINALIS WHOLE; SODIUM HYDROXIDE

EAR FLUSH - ADVANCED OTIC CLEANSER

ACTIVE INGREDIENTS:

Ketoconazole.......0.2% (Antifungal)

INDICATIONS:

Medicated cleansing and flushing solution to support topical conditions responsive to Ketoconazole.

WARNINGS:

For external use only. Not for human use. KEEP OUT OF REACH OF CHILDREN. When using this product, avoid contact with eyes and mucous membranes. If condition worsens, or irritation occurs, stop use and ask your veterinarian.

DIRECTIONS:

FOR USE ON EARS - Apply solution to the ear canal and with rm but gentle pressure, massage the base of the ear. Use an absorbent material to clean any excess solution and wipe away debris. Do not allow the animal to lick the treated area until dry to prevent ingestion. Wash hands after use.

STORAGE:

Store at room temperature - 68F to 77F (20°C-25°C). Protect from freezing or excessive heat.

FIRST AID:

If eye contact occurs or skin irritation develops, rinse thoroughly with water, discontinue use, and if irritation persists, contact a veterinarian.
If large quantities of this material are swallowed, contact the poison control center immediately!

INACTIVE INGREDIENTS:

Water, Polysorbate 20, Propylene Glycol, Aloe Barbadensis Leaf Juice, Ethoxydiglycol, Glycerin, Lactic Acid, Benzyl Alcohol, Boric Acid,
Calendula Ocinalis, Sodium Hydroxide